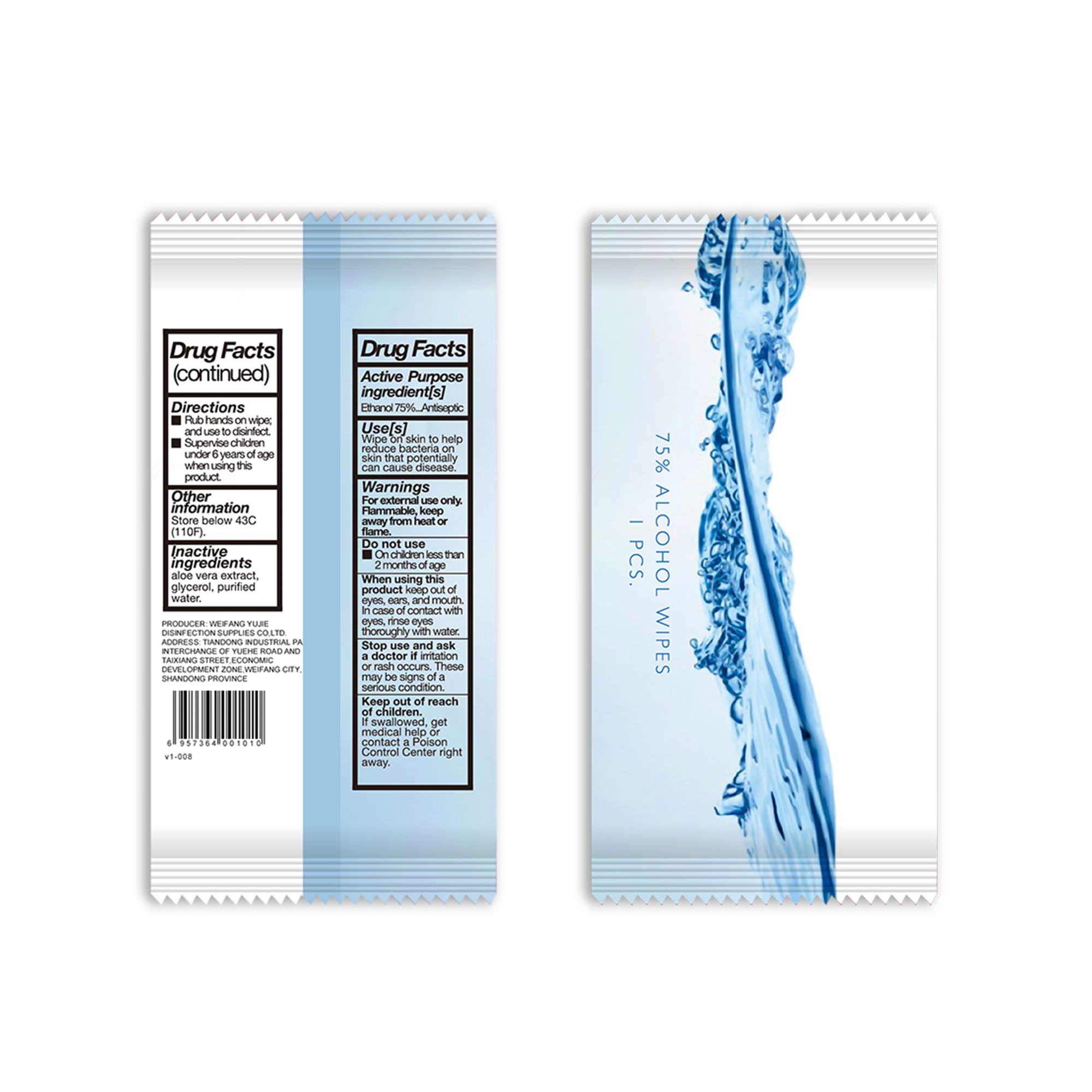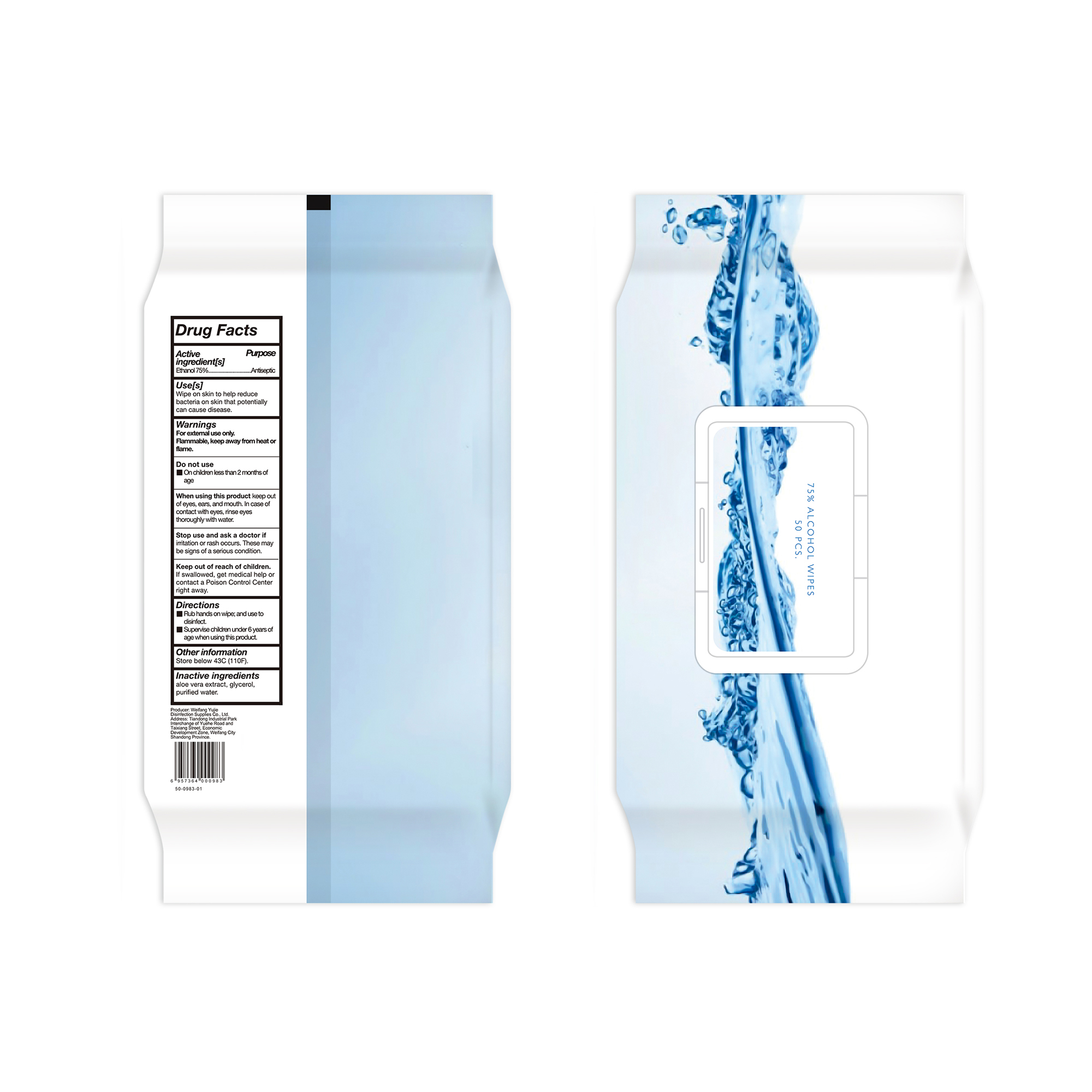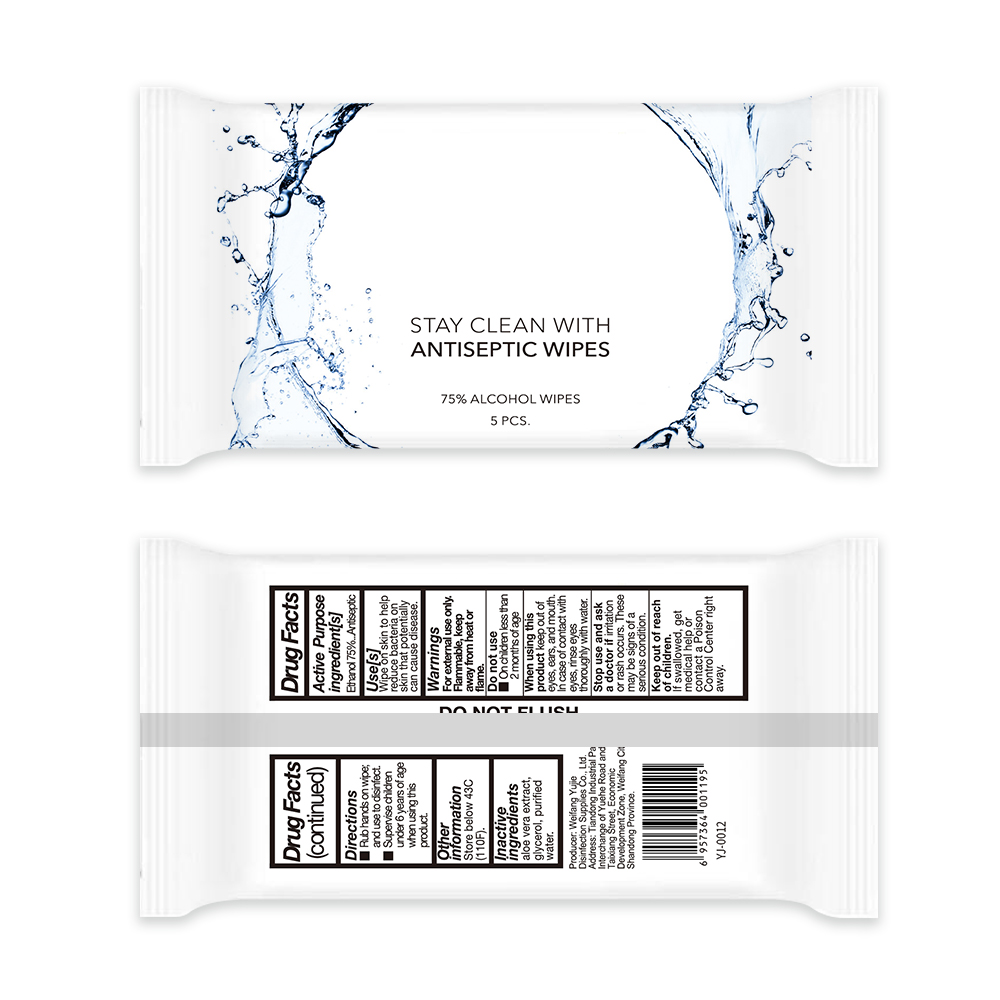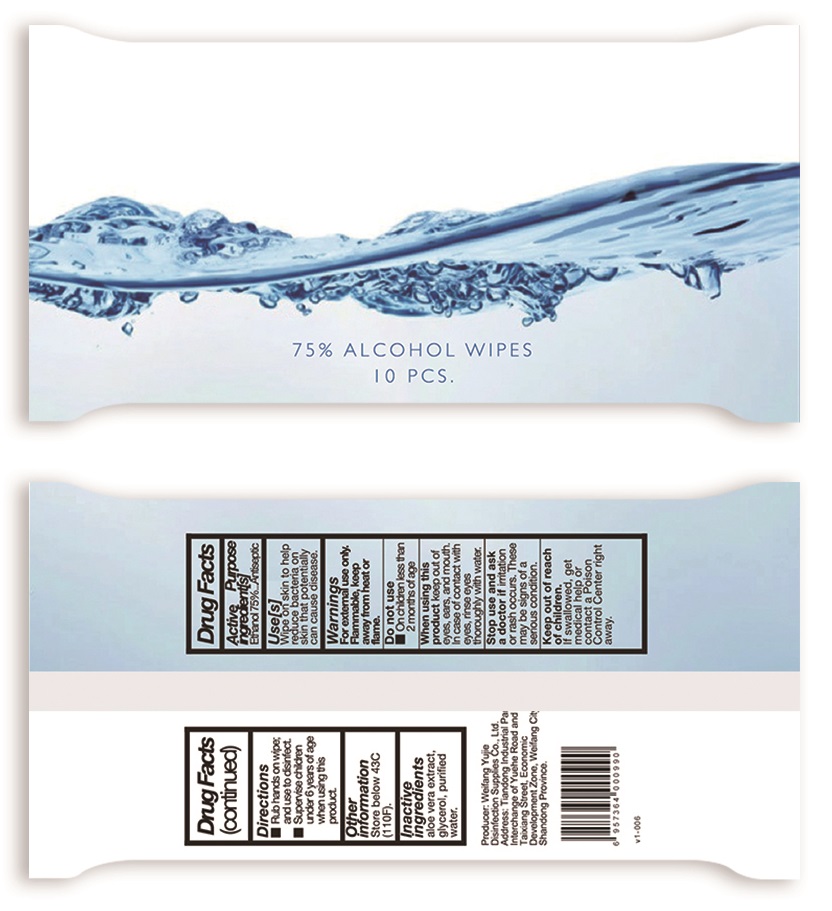 DRUG LABEL: ALCOHOL WIPES
NDC: 78959-002 | Form: CLOTH
Manufacturer: Weifang Yujie Disinfectant Co. , Ltd.
Category: otc | Type: HUMAN OTC DRUG LABEL
Date: 20200914

ACTIVE INGREDIENTS: ALCOHOL 75 mL/100 1
INACTIVE INGREDIENTS: GLYCERIN; ALOE VERA LEAF; WATER

78959-002
ALCOHOL WIPES

Active Ingredient

Ethanol 75%

Purpose

Antiseptic

Use

Wipe on skin to help reduce bacteria on skin that potentially can cause diseas

Warnings

For external use only
Flammable, keep away from heat or fame

Do not use

On children less than 2 montns of age

When using this product

keep out of eyes, ears, and mouth. In case of contact with eyes, rinse eyes thoroughly with water

Stop use and ask doctor

irritation or rash occurs, These may be signs of a senous condition.

Keep out of reach of children

If swallowed, get medical help or contact a poison control center right away

Directions

Rub hands on wipe
and use to disinfect
Supervise children under 6 years of age when using ths product.

Other information

Store below 43C (110F

Inactive Ingredients

aloe vera extract, glycerol, purified water.